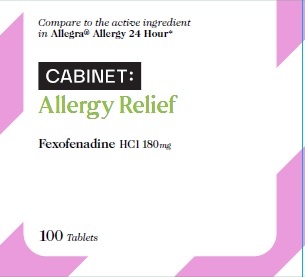 DRUG LABEL: Fexofenadine Hydrochloride
NDC: 68210-4090 | Form: TABLET, FILM COATED
Manufacturer: SPIRIT PHARMACEUTICALS LLC
Category: otc | Type: HUMAN OTC DRUG LABEL
Date: 20241213

ACTIVE INGREDIENTS: FEXOFENADINE HYDROCHLORIDE 180 mg/1 1
INACTIVE INGREDIENTS: CROSCARMELLOSE SODIUM; ANHYDROUS LACTOSE; STARCH, CORN; HYPROMELLOSES; LACTOSE MONOHYDRATE; FERRIC OXIDE RED; STEARIC ACID; FERRIC OXIDE YELLOW; SILICON DIOXIDE; POLYETHYLENE GLYCOL, UNSPECIFIED; TITANIUM DIOXIDE

Fexofenadine Hydrochloride Tablets, 180 mg

Active ingredient (in each caplet)

Fexofenadine HCl USP 180 mg

Purpose

Antihistamine

Uses

temporarily relieves these symptoms due to hay fever or other upper respiratory allergies:

■ runny nose

■ sneezing

■ itchy, watery eyes

■ itching of the nose or throat

Do not use if

you have ever had an allergic reaction to this product or any of its ingredients.

Ask a doctor before use if you have

kidney disease. Your doctor should determine if you need a different dose.

When using this product

■ do not take more than directed

■ do not take at the same time as aluminum or magnesium antacids

■ do not take with fruit juices (see Directions)

Stop use and ask a doctor if

an allergic reaction to this product occurs. Seek medical help right away.

If pregnant and breast-feeding,

ask a health professional before use.

Keep out of reach of children

In case of overdose, get medical help or contact a Poison Control Center right away. 1-800-222-1222

Directions

adults and children 12 years of age and over: take one 180mg tablet with water once a day

do not take more than 1 tablet in 24 hours

children under 12 years of age: do not use

adults 65 years of age and older: ask a doctor

consumers with kidney disease: ask a doctor

Other information

■ store between 20°and 25°C (68°and 77°F)

■ protect from excessive moisture

Inactive ingredients

anhydrous lactose, colloidal silicon dioxide, corn starch, croscarmellose sodium, hypromellose, lactose monohydrate, polyethylene glycol, pregelatinized starch (maize), red iron oxide, stearic acid, titanium dioxide and yellow iron oxide.

Questions or comments?

1-888-333-9792

PRINCIPAL DISPLAY PANEL

Compare to the active ingredient
in Allegra® Allergy 24 Hour†

ALLERGY RELIEF

Fexofenadine HCl
tablets USP 180 mg /
antihistamine

100 TABLETS